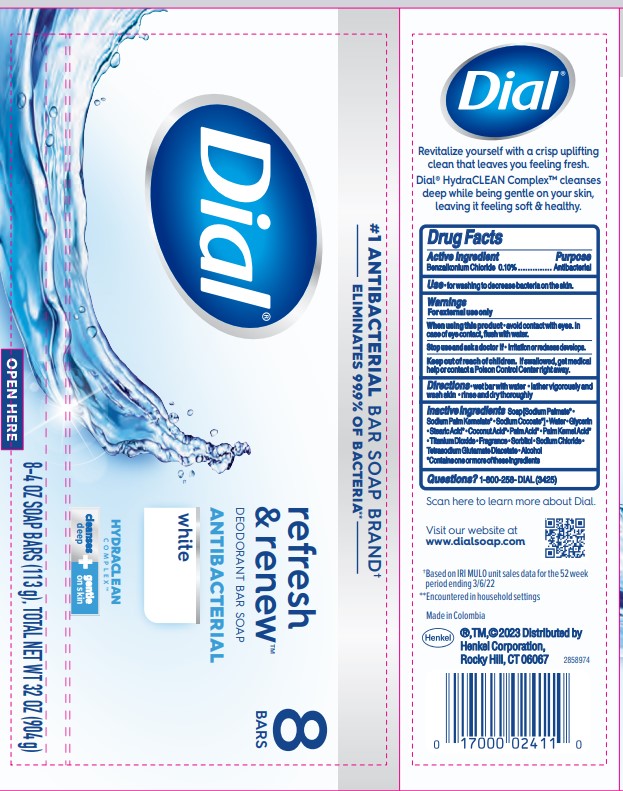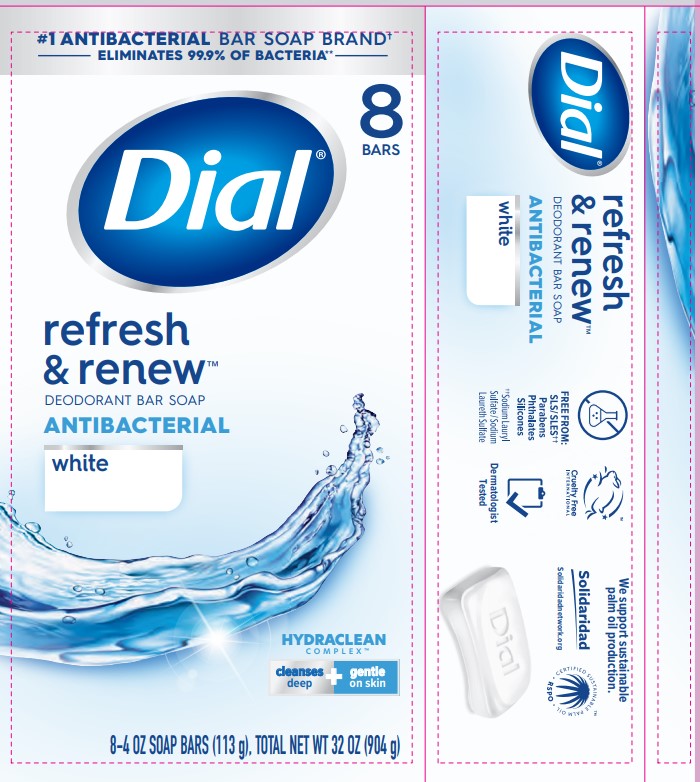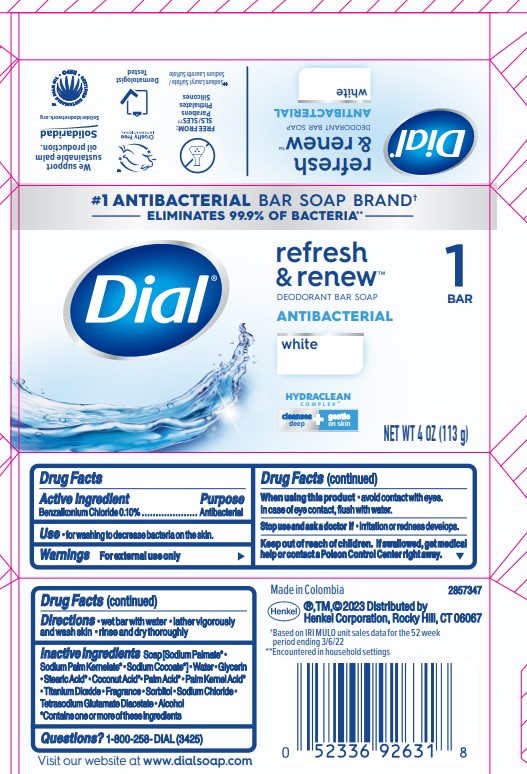 DRUG LABEL: Dial Antibacterial Bar
NDC: 54340-278 | Form: SOAP
Manufacturer: Henkel Corporation
Category: otc | Type: HUMAN OTC DRUG LABEL
Date: 20251113

ACTIVE INGREDIENTS: BENZALKONIUM CHLORIDE 0.1 g/100 g
INACTIVE INGREDIENTS: SORBITOL 0.5525 g/100 g; TITANIUM DIOXIDE 0.8 g/100 g; SODIUM CHLORIDE 0.3898 g/100 g; SODIUM PALM KERNELATE 11.01 g/100 g; GLYCERIN 8.1 g/100 g; ALCOHOL 0.01 g/100 g; SODIUM PALMATE 61.87 g/100 g; TETRASODIUM GLUTAMATE DIACETATE 0.058 g/100 g; STEARIC ACID 2.4365 g/100 g

Dial Antibacterial Deodarant Bar Soap - White
Dial Refresh & Renew Deodorant Bar Soap Antibacterial White

Active Ingredient

Benzalkonium Chloride 0.10%

Purpose

Antibacterial

Uses

- for washing to decrease the bacteria on the skin

Warnings

For external use only

When using this product

- avoid contact with eyes. In case of eye contact, flush with water.

Stop using and ask doctor if

- irritation or redness develops

Keep out of reach of children.

If swallowed, get medical help or contact Poison Control Center right away.

Directions

- wet bar with water
- lather vigorously and wash skin
- rinse and dry thoroughly

Inactive ingredients

Sodium Palmate
Water
Sodium Palm Kernelate

Sodium Cocoate

Coconut Acid

Palm Kernel acid

Palm Acid

Stearic Acid
Glycerin
Stearic Acid
CI 77891 (Titanium Dioxide)
Fragrance
Sorbitol
Sodium Chloride
Tetrasodium Glutamate Diacetate
Alcohol

CONTAINS ONE OR MORE OF THESE INGREDIENTS

Questions?

1-800-258-DIAL (3425)